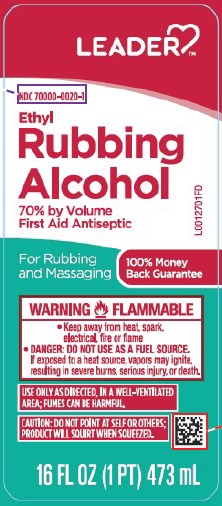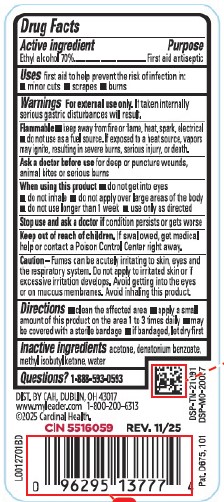 DRUG LABEL: Ethyl Rubbing Alcohol
NDC: 70000-0020 | Form: LIQUID
Manufacturer: Cardinal Health, 110 dba Leader
Category: otc | Type: HUMAN OTC DRUG LABEL
Date: 20260129

ACTIVE INGREDIENTS: ALCOHOL 70 mL/100 mL
INACTIVE INGREDIENTS: ACETONE; DENATONIUM BENZOATE; METHYL ISOBUTYL KETONE; WATER

Leader 876.002/876AC
Ethyl Rubbing Alcohol 70%

Active ingredient

Ethyl alcohol 70%

Purpose

First aid antiseptic

Uses

first aid to help prevent the risk of infection in:

- minor cuts
- scrapes
- burns

Warnings

For external use only. If taken internally serious gastric disturbances will result.

Flammable

- keep away from fire or flame, heat spark, electrical
- do not use as a fuel source. If exposed to a heat source, vapors may ignite, resulting in severe burns, serious injury, or death.

Ask a doctor before use

for deep or puncture wounds, animal bites or serious burns

When using this product

- do not get into eyes
- do not inhale
- do not apply over large areas of the body
- do not use longer than 1 week
- use only as directed

Stop use and ask a doctor if

condition persists or gets worse

Keep out of reach of children.

If swallowed, get medical help or contact a Poison Control Center right away.

Caution

Fumes can be acutely irritating to skin, eyes and the respiratory system. Do not apply to irritated skin or if excessive irritation develops. Avoid getting into the eyes or on mucous membranes. Avoid inhaling this product.

Directions

- clean the affected area
- apply a small amount of this product on the area 1 to 3 times daily
- may be covered with a sterile bandage
- if bandaged, let dry first

Inactive ingredients

acetone, denatonium benzoate, methyl isobutyl ketone, water

Questions?

1-888-593-0593

Adverse event

DSP-TN-21091 DSP-MO-20087

DIST. BY CAH DUBLIN, OH 43017

www.myleader.com

1-800-200-6313

©2025 Cardinal Health.

CIN 5516059 REV. 11/25

Pat. D675, 101

Principal Panel Display

LEADER™

NDC 70000-0020-1

Ethyl Rubbing Alcohol

70% by Volume

First Aid Antiseptic

For Rubbing and Massaging

100% Money Back Guarantee

WARNING FLAMMABLE

- Keep away from heat, spark, electrical, fire or flame
- DANGER: DO NOT USE AS A FUEL SOURCE. If exposed to a heat source, vapors may ignite, resulting in sever burns, serious injury, or death.

USE ONLY AS DIRECTED, IN A WELL-VENTILATED AREA; FUMES CAN BE HARMFUL.

CAUTION: DO NOT POINT AT SELF OR OTHERS; PRODUCT WILL SQUIRT WHEN SQUEEZED.

16 FL OZ (1 PT) 473 mL